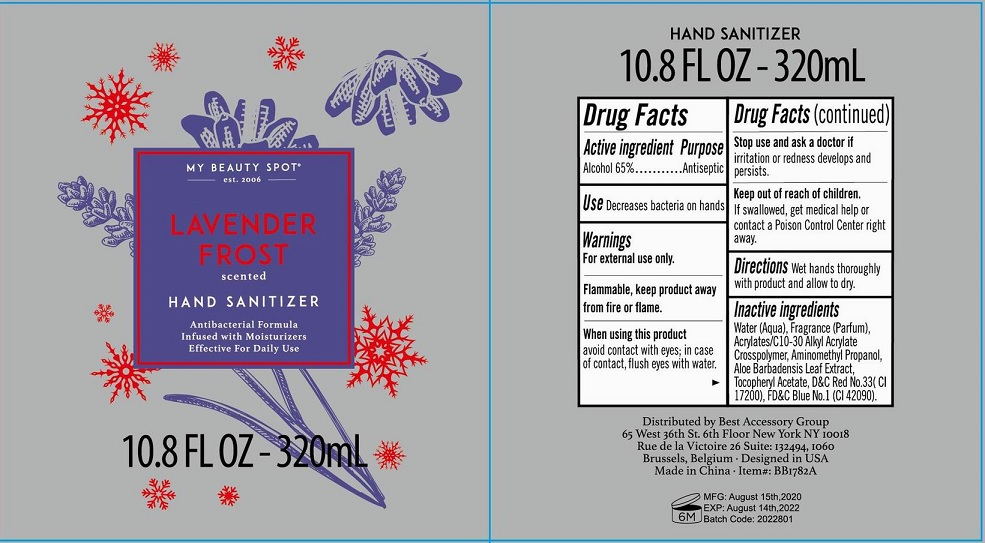 DRUG LABEL: Lavender Frost Scented Antibacterial Hand Sanitizer
NDC: 56136-205 | Form: GEL
Manufacturer: Ganzhou Olivee Cosmetic Co., Ltd.
Category: otc | Type: HUMAN OTC DRUG LABEL
Date: 20200923

ACTIVE INGREDIENTS: ALCOHOL 65 mL/100 mL
INACTIVE INGREDIENTS: water; CARBOMER COPOLYMER TYPE A; AMINOMETHYLPROPANOL; GLYCERIN; .ALPHA.-TOCOPHEROL ACETATE, D-; FD&C BLUE NO. 1; D&C RED NO. 33

hand sanitizer

Active ingredient

Alcohol 65%

Purpose

Antiseptic

USE

Decrease bacteria on hands

Warnings

For external use only.

When using this product

avoid contact with eyes; in case of contact, flush eyes with water.

Stop use and ask a doctor if

- irritation and redness develops and persists.

Keep out of reach of children.

If swallowed, get medical help or contact a Poison Control Center right away.

Directions

Wet hands thoroughly with product and allow to dry.

Inactive ingredients

Water (Aqua), Acrylates/c 10-30 Alkyl Acrylate Crosspolymer, Aminomethyl Propanol, Fragrace (Parfum), D&C Red No. 33 (Cl 17200), FD&C Blue No. 1 (Cl 42090).